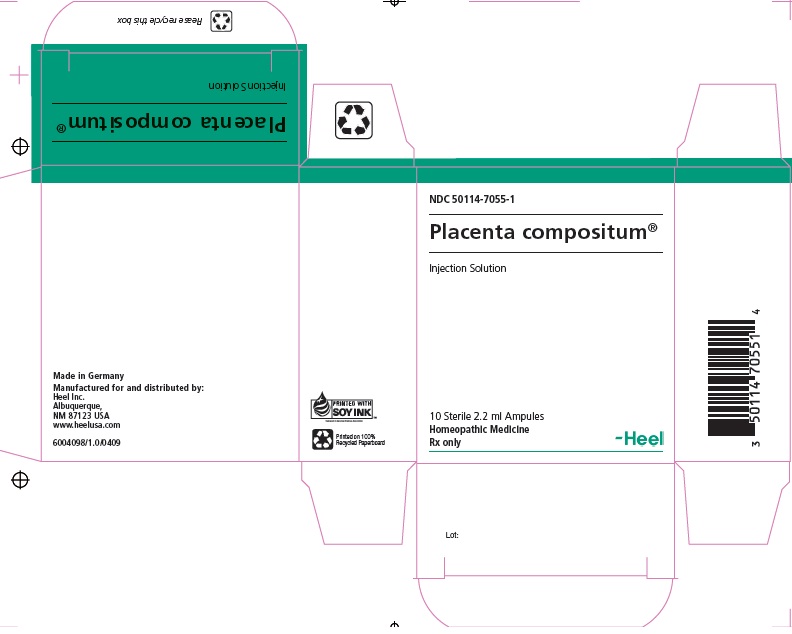 DRUG LABEL: Placenta Compositum
NDC: 50114-7055 | Form: INJECTION
Manufacturer: Heel Inc
Category: homeopathic | Type: HUMAN PRESCRIPTION DRUG LABEL
Date: 20120514

ACTIVE INGREDIENTS: HORSE CHESTNUT 4 [hp_X]/2.2 mL; LACTIC ACID, L- 4 [hp_X]/2.2 mL; CLAVICEPS PURPUREA SCLEROTIUM 4 [hp_X]/2.2 mL; CUPRIC SULFATE 6 [hp_X]/2.2 mL; MELILOTUS OFFICINALIS TOP 6 [hp_X]/2.2 mL; SUS SCROFA PLACENTA 6 [hp_X]/2.2 mL; SOLANUM NIGRUM WHOLE 6 [hp_X]/2.2 mL; STROPHANTHUS HISPIDUS SEED 6 [hp_X]/2.2 mL; SUS SCROFA EMBRYO 8 [hp_X]/2.2 mL; SODIUM PYRUVATE 8 [hp_X]/2.2 mL; SUS SCROFA VEIN 8 [hp_X]/2.2 mL; SUS SCROFA ARTERY 10 [hp_X]/2.2 mL; SUS SCROFA UMBILICAL CORD 10 [hp_X]/2.2 mL; TOBACCO LEAF 10 [hp_X]/2.2 mL; VIPERA BERUS VENOM 10 [hp_X]/2.2 mL; BARIUM CARBONATE 13 [hp_X]/2.2 mL; LEAD IODIDE 18 [hp_X]/2.2 mL
INACTIVE INGREDIENTS: SODIUM CHLORIDE

Placenta Compositum 2.2 ml Injection

DESCRIPTION

Injection Solution Ingredient Information: Each 2.2 ml ampule contains: Aesculus hippocastanum 4X, Sarcolacticum acidum 4X, Secale cornutum 4X, Cuprum sulphuricum 6X, Melilotus officinalis 6X, Placenta suis 6X, Solanum nigrum 6X, Strophanthus hispidus 6X, Embryo suis 8X, Natrum pyruvicum 8X, Vena suis 8X, Arteria suis 10X, Funiculus umbilicalis suis 10X, Tabacum 10X, Vipera berus 10X, Baryta carbonica 13X, Plumbum iodatum 18X 22 mcl each. Inactive ingredient: Sterile isotonic sodium chloride
solution

INDICATION AND USAGE

Placenta compositum Injection Solution is indicated for stimulation of metabolic functions of the peripheral circulation of the blood as well as for a revitalizing and stimulating effect on the liver and peripheral vascular system.
Placenta compositum Injection Solution is classified as a homeopathic combination drug.
Botanical ingredients:
Aesculus hippocastanum (horse chestnut)
Melilotus officinalis (yellow sweet clover)
Secale cornutum (rye ergot)
Solanum nigrum (black nightshade)
Strophanthus hispidus (Strophanthus)
Tabacum (tobacco)
Mineral ingredients:
Baryta carbonica (barium carbonate)
Cuprum sulphuricum (copper sulfate)
Natrum pyruvicum (sodium pyruvate)
Plumbum iodatum (lead iodide)
Sarcolacticum acidum (L-lactic acid)
Animal-derived ingredients
Arteria suis (porcine artery)
Embryo suis (porcine embryo)
Funiculus umbilicalis suis (porcine umbilical cord)
Placenta suis (porcine placenta)
Vena suis (porcine vein)
Vipera berus (common viper)

DOSAGE AND ADMINISTRATION

The dosage schedules listed below can be used as a general guide for the administration of Placenta compositum Injection Solution. Placenta compositum Injection Solution shows individual differences in clinical response. Therefore, the dosage for each patient should be individualized according to the patient’s response to therapy.
Adults and children 7 years and older: in acute disorders, 1 ampule per day, otherwise 1 ampule, 1 to 3 times per week IM/SC/IV/ID. Children ages 2 to 6 receive ½ the adult dosage.
Discard unused solution.

WARNINGS

Warnings and Precautions
If pain persists or worsens, if new symptoms occur, or if redness or swelling is present, the patient should be carefully re-evaluated because these could be signs of a serious condition.
Pregnancy Category C. Animal reproduction studies have not been conducted with this drug. It is also not known whether this drug can cause fetal harm when administered to a pregnant woman or can affect reproduction capacity. This drug should be given to a pregnant woman only if clearly needed.
To report SUSPECTED ADVERSE REACTIONS, contact Heel Inc. at 1.800.920.9203 or info@heelusa.com or FDA at 1-800-FDA-1088 or www.fda.gov/medwatch